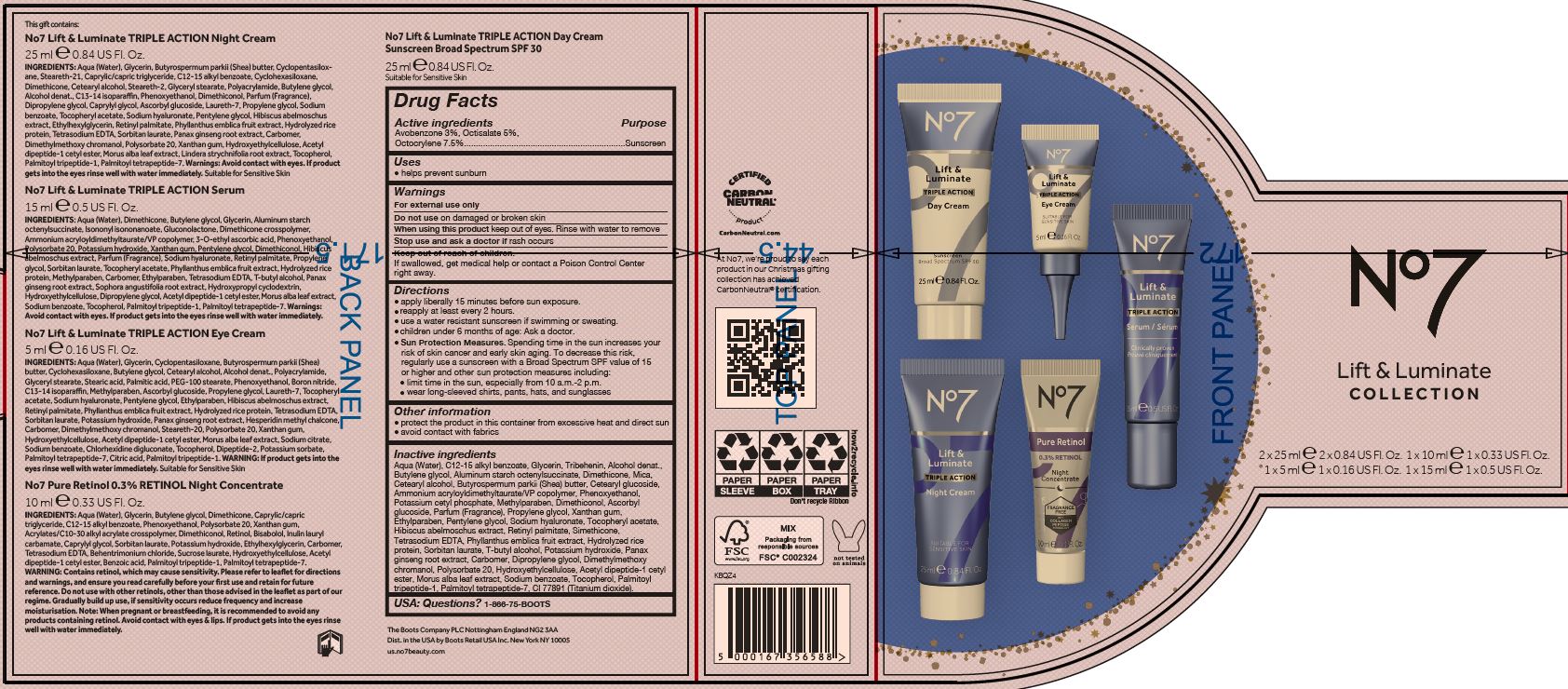 DRUG LABEL: No7 Lift and Luminate Triple Action Day Cream SPF 30
NDC: 11489-190 | Form: CREAM
Manufacturer: BCM Ltd
Category: otc | Type: HUMAN OTC DRUG LABEL
Date: 20220624

ACTIVE INGREDIENTS: AVOBENZONE 0.75 g/25 g; OCTOCRYLENE 1.875 g/25 g; OCTISALATE 1.25 g/25 g
INACTIVE INGREDIENTS: WATER; GLYCERIN; ALUMINUM STARCH OCTENYLSUCCINATE; DIMETHICONE; MICA; ALKYL (C12-15) BENZOATE; CETEARYL GLUCOSIDE; TRIBEHENIN; PENTYLENE GLYCOL; AMMONIUM ACRYLOYLDIMETHYLTAURATE/VP COPOLYMER; PHENOXYETHANOL; CETOSTEARYL ALCOHOL; SHEA BUTTER; BUTYLENE GLYCOL; METHYLPARABEN; DIMETHICONOL (40 CST); ETHYLPARABEN; XANTHAN GUM; SODIUM LAUROYL LACTYLATE; PHYLLANTHUS EMBLICA FRUIT; VITAMIN A PALMITATE; ASCORBYL GLUCOSIDE; EDETATE SODIUM; TERT-BUTYL ALCOHOL; PROPYLENE GLYCOL; POLYSORBATE 20; DIPROPYLENE GLYCOL; DIMETHYLMETHOXY CHROMANOL; POTASSIUM HYDROXIDE; TOCOPHEROL; MORUS ALBA LEAF; SODIUM BENZOATE; TITANIUM DIOXIDE; PALMITOYL TETRAPEPTIDE-7; PALMITOYL TRIPEPTIDE-1; POTASSIUM CETYL PHOSPHATE; HYALURONATE SODIUM; ALCOHOL; SILICON; SORBITAN MONOLAURATE; HYDROXYETHYL CELLULOSE (100 MPA.S AT 2%); CARBOXYPOLYMETHYLENE; ACETYL TYROSYLARGININE CETYL ESTER; ABELMOSCHUS MOSCHATUS WHOLE; ASIAN GINSENG

No7 Lift and Luminate Triple Action Day Cream Sunscreen Broad Spectrum SPF 30

Carton Active Ingredients Section

Active ingredients

Avobenzone 3%

Octisalate 5%

Octocrylene 7.5%

Uses

helps prevent sunburn

Warnings

For external use only

Do not use on damaged or broken skin

When using this product keep out of eyes. Rinse with water to remove.

Ask a doctor

Stop use and ask a doctor if rash occurs

Keep out of reach of children

If swallowed, get medical help or contact a Poison Control Center right away.

Directions

apply liberally 15 minutes before sun exposure.

reapply at least every 2 hours.

use a water resistant sunscreen if swimming or sweating.

children under 6 months of age: Ask a doctor.

Sun Protection Measures. Spending time in the sun increases your risk of skin cancer and early skin aging. To decrease this risk, regularly use a sunscreen with a Broad Spectrum SPF value of 15 or higher and other sun protection measures including:

Limit time in the sun, especially from 10 a.m - 2 p.m.

wear long-sleeved shirts, pants, hats and sunglasses

Storage

Other information

protect the product in this container from excessive heat and direct sun

avoid contact with fabrics

Inactive ingredients

Aqua (Water), C12-15 alkyl benzoate, Glycerin, Tribehenin, Alcohol denat., Butylene glycol, Aluminum starch octenylsuccinate, Dimethicone, Mica, Cetearyl alcohol, Butyrospermum parkii (Shea) butter, Cetearyl glucoside, Ammonium acryloyldimethyltaurate/VP copolymer, Phenoxyethanol, Potassium cetyl phosphate, Methylparaben, Dimethiconol, Ascorbyl glucoside, Parfum (Fragrance), Propylene glycol, Xanthan gum, Ethylparaben, Pentylene glycol, Sodium hyaluronate, Tocopheryl acetate, Hibiscus abelmoschus extract, Retinyl palmitate, Simethicone, Tetrasodium EDTA, Phyllanthus emblica fruit extract, Hydrolyzed rice protein, Sorbitan laurate, T-butyl alcohol, Potassium hydroxide, Panax ginseng root extract, Carbomer, Dipropylene glycol, Dimethylmoethoxy chromanol, Polysorbate 20, Hydroxyethylcellulose, Acetyl dipeptide-1 cetyl ester, Morus alba leaf extract, Sodium benzoate, Tocopherol, Palmitoyl tripeptide-1, Palmitoyl tetrapeptide-7, CI77891 (Titanium dioxide).

PATIENT COUNSELING INFORMATION

USA: Questions? 1-866-75-BOOTS

Made in the UK

The Boots Company PLC

Nottingham England NG2 3AA.

Dist. in the USA by Boots Retail USA Inc. New York NY 10005

www.no7beauty.com

Description

No7 Lift & Luminate COLLECTION

25 ml e 0.84 US Fl. Oz.

Box